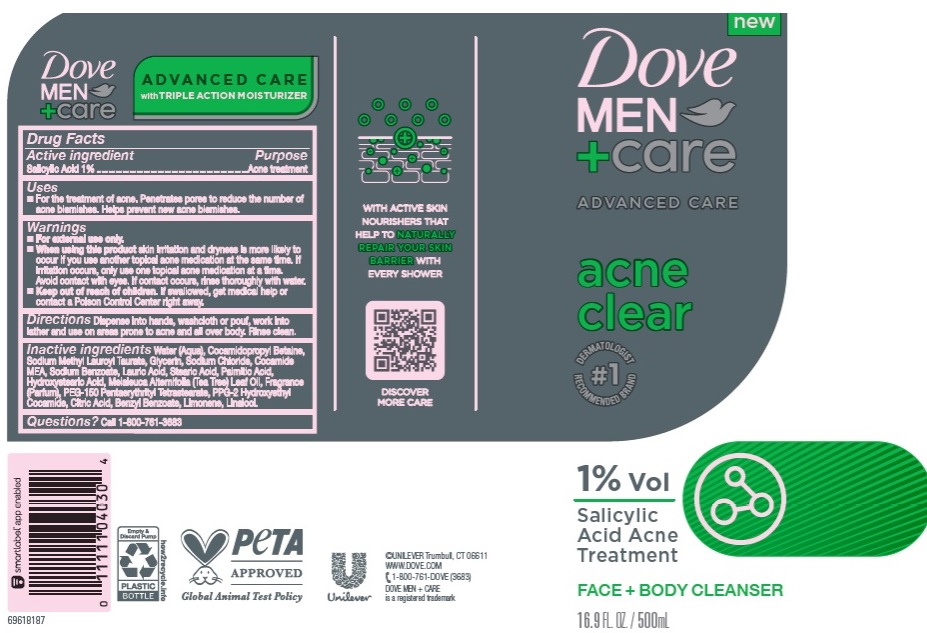 DRUG LABEL: Dove
NDC: 64942-2093 | Form: LIQUID
Manufacturer: CONOPCO Inc. d/b/a Unilever
Category: otc | Type: HUMAN OTC DRUG LABEL
Date: 20241107

ACTIVE INGREDIENTS: SALICYLIC ACID 1 g/100 mL
INACTIVE INGREDIENTS: WATER; GLYCERIN; SODIUM LAUROYL METHYL TAURATE; COCAMIDOPROPYL BETAINE; COCO MONOETHANOLAMIDE; SODIUM CHLORIDE; SODIUM BENZOATE; 12-HYDROXYSTEARIC ACID; STEARIC ACID; TEA TREE OIL; PALMITIC ACID; PEG-150 PENTAERYTHRITYL TETRASTEARATE; LINALOOL, (+/-)-; LIMONENE, (+)-; PPG-2 HYDROXYETHYL COCAMIDE; CITRIC ACID MONOHYDRATE; BENZYL BENZOATE; LAURIC ACID

Dove Men + Care Advanced Acne Clear Face + Body Cleanser

Active ingredient

Salicylic Acid (1%)

Purpose

Acne Treatment

Uses

For the treatment of acne
Penetrates pores to reduce the number of acne blemishes
Helps prevent new acne blemishes

Warnings

For external use only
When using this product skin irritation and dryness is more likely to occur if you use another topical acne medication at the same time. If irritation occues, only use one topical acne medication at a time. Avoid contact with eyes. If contact occurs, rinse thoroughly with water.

Keep out of reach of children
If swallowed, get medical help or contact a Poison Control Center right away.

Directions

Dispense into hands, washcloth or pouf, work into lather and use on areas prone to acne and all over body. Rinse clean.

Inactive ingredients

Water (Aqua), Cocamidopropyl Betaine, Sodium Methyl Lauroyl Taurate, Glycerin, Sodium Chloride, Cocamide MEA, Sodium Benzoate, Lauric Acid, Stearic Acid, Palmitic Acid, Hydroxystearic Acid, Melaleuca Alernifolia (Tea Tree) Leaf Oil, Fragrance (Parfum), PEG-150 Pentaerythrityl Tetrastearate, PPG-2 Hydroxyethyl Cocomide, Citric Acid, Benzyle Benzoate, Limonene, Linalool,

Questions?

Call 1-800-761-3683